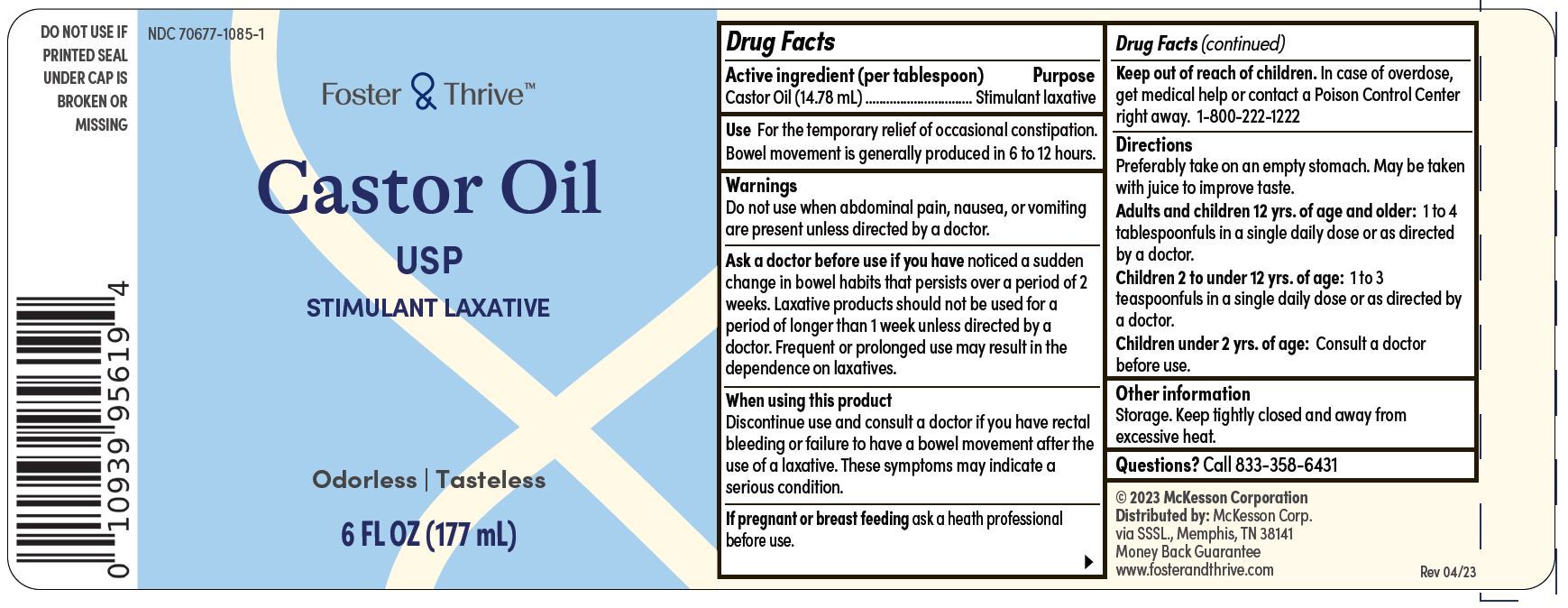 DRUG LABEL: Foster and Thrive Castor Oil
NDC: 70677-1085 | Form: LIQUID
Manufacturer: Strategic Sourcing Services, LLC
Category: otc | Type: HUMAN OTC DRUG LABEL
Date: 20241230

ACTIVE INGREDIENTS: CASTOR OIL 1 mg/1 mL
INACTIVE INGREDIENTS: WATER

Foster & Thrive Castor Oil

Drug Facts

Active Ingredient

Castor Oil

Purpose

Stimulant Laxative

Use

For the temporary relief of occasional constipation. Bowel movement is generally produced in 6 to 12 hours.

Warings

Do not use when abdominal pain, nausea, or vomiting are present unless directed by a doctor.

Ask a doctor before use

if you have noticed a sudden change in bowel habits that persists over a period of 2 weeks. Laxative products should not be used for a period of longer than 1 week unless directed by a doctor. Frequent or prolonged use may result in the dependence on laxatives.

When using this product

Discontinue use and consult a doctor if you have rectal bleeding or failure to have a bowel movement after the use of a laxative. These symptoms may indicate a serious condition.

If pregnant or breast feeding

ask a health professional before use

Keep out of reach of children.

In case of accidental overdose, seek profssional assistance or contact a Poison Control Center right away. 1-800-222-1222

Directions

Preferably take on an empty stomach. May be taken with juice to improve taste.

Adults and children 12 yrs. of age and older: 1 to 4 tablespoonfuls in a single daily dose or as directed by a doctor.

Children 2 to under 12 yrs. of age: 1 to 3 tablespoonfuls in a single dose or as directed by a doctor.

Children under 2 yrs. of age: Consult a doctor before use.

WARNINGS:

Do not use if printed seal under cap is broken or missing

Other Information

storage. Keep tightly closed and away from excessive heat.

Inactive Ingredient

None